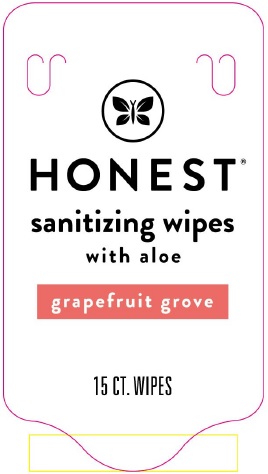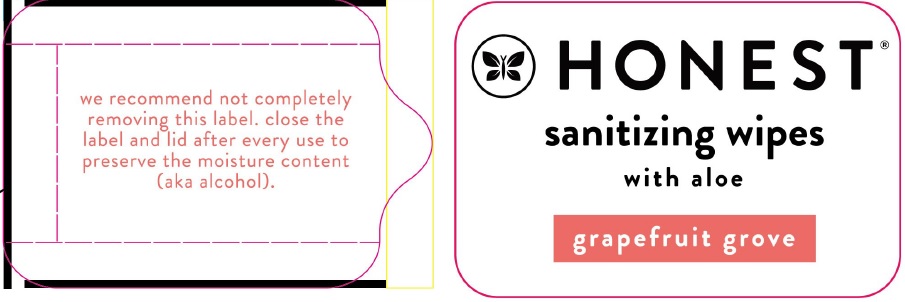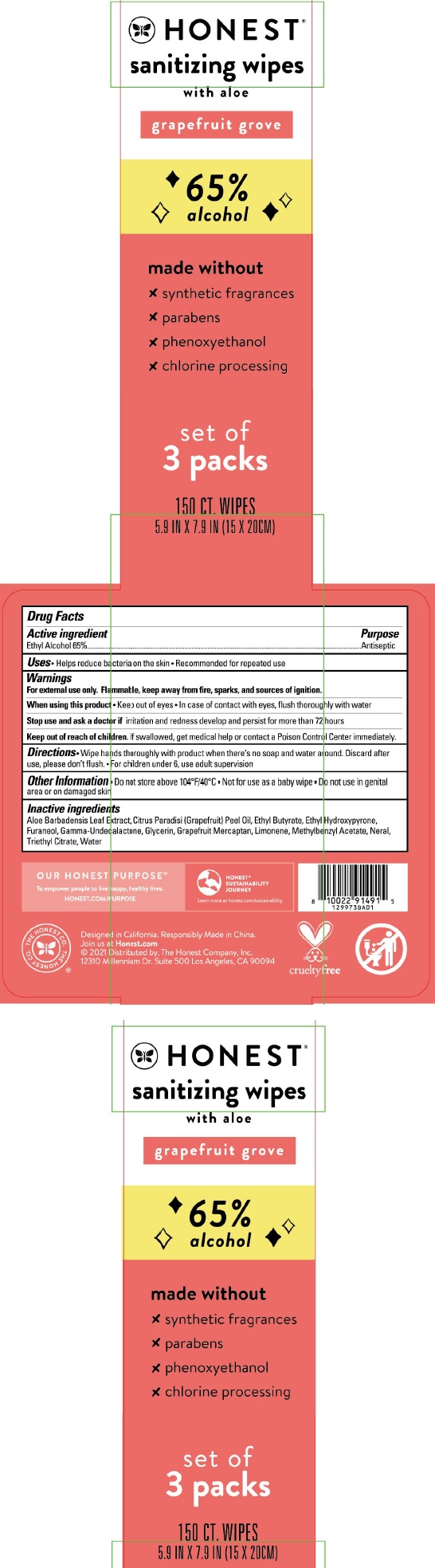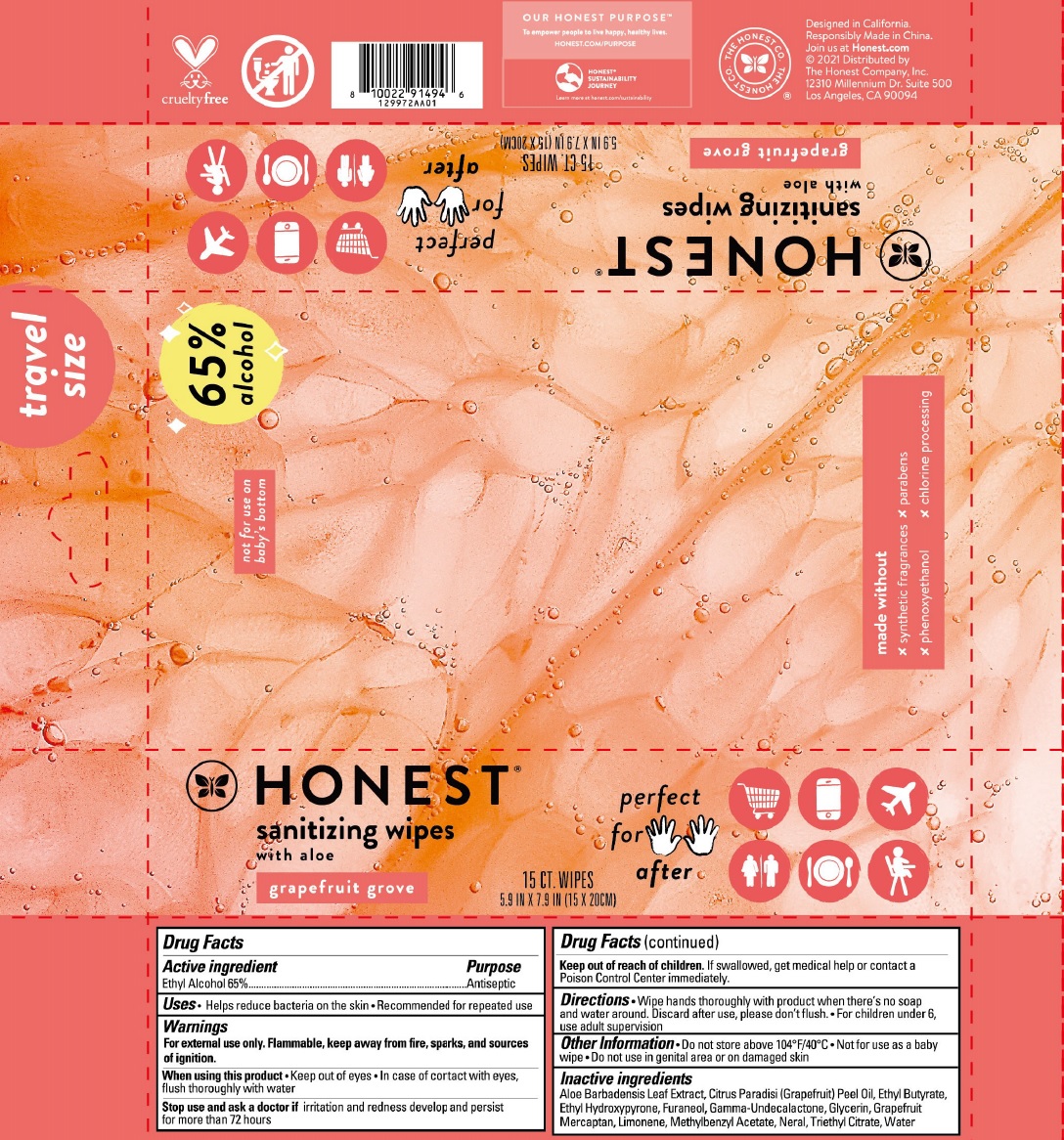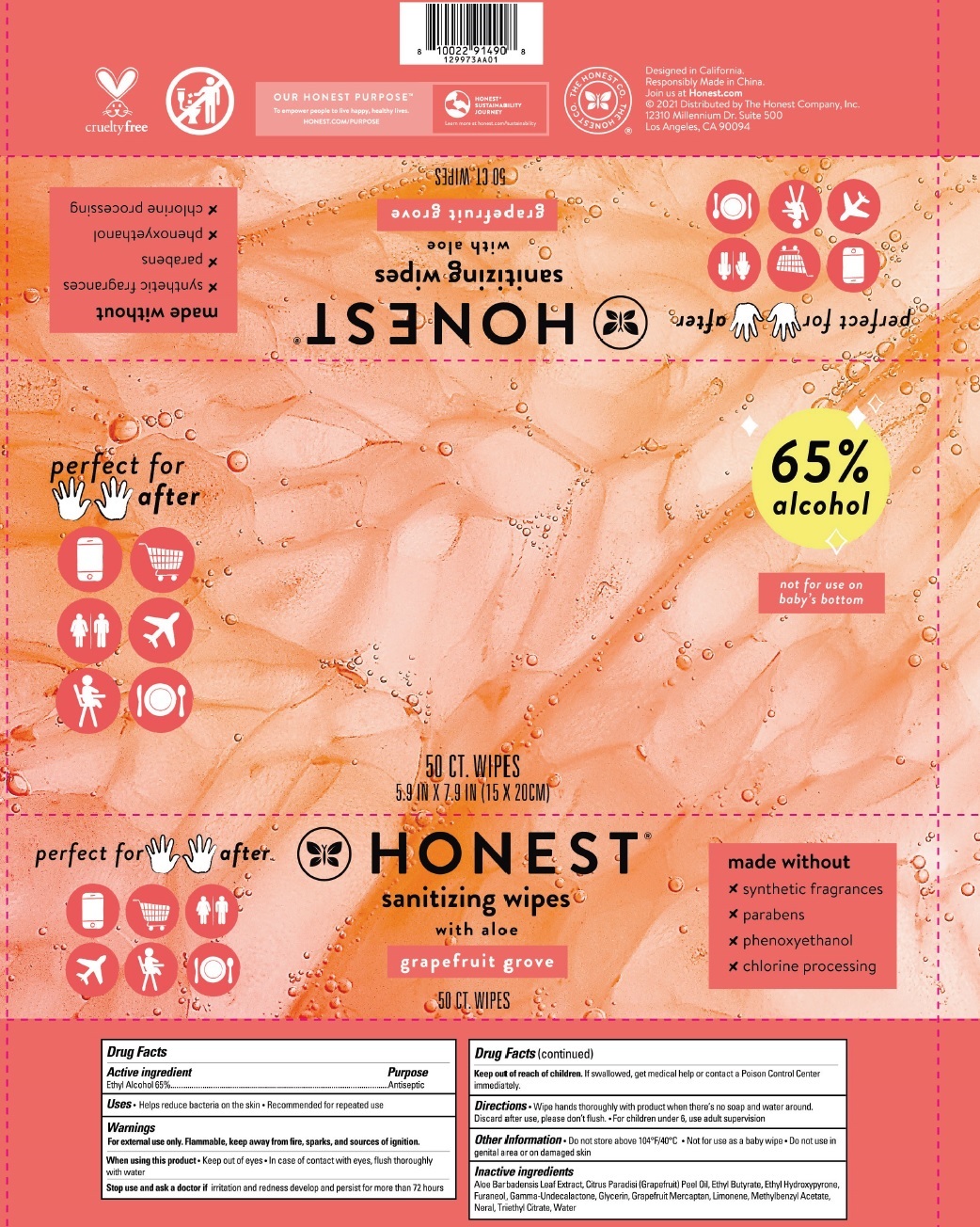 DRUG LABEL: Sanitizing wipes with aloe Grapefruit Grove
NDC: 69366-317 | Form: CLOTH
Manufacturer: The Honest Company
Category: otc | Type: HUMAN OTC DRUG LABEL
Date: 20231219

ACTIVE INGREDIENTS: ALCOHOL 65 mL/100 mL
INACTIVE INGREDIENTS: ALOE VERA LEAF; GRAPEFRUIT OIL; ETHYL BUTYRATE; ETHYL MALTOL; DIMETHYLHYDROXY FURANONE; .GAMMA.-UNDECALACTONE; GLYCERIN; 1-P-MENTHENE-8-THIOL; LIMONENE, (+)-; METHYLBENZYL ACETATE; NERAL; TRIETHYL CITRATE; WATER

Sanitizing wipes with aloe Grapefruit Grove

Active ingredient

Ethyl Alcohol 65%

Purpose

Antiseptic

Uses

- Helps reduce bacteria on the skin
- Recommended for repeated use

Warnings

For external use only. Flammable, keep away from fire, sparks, and sources or ignition.

When using this product

- Keep out of eyes
- In case of contact with eyes, flush thoroughly with water

Stop use and ask a doctor if

irritation and redness develop and persist for more than 72 hours

Keep out of reach of children.

If swallowed, get medical help or contact a Poison Control Center immediately.

Directions

- Wipe hands thoroughly with product when there's no soap and water around. Discard after use, please don't flush.
- For children under 6, use adult supervision

Other Information

- Do not store above 104°F/40°C
- Not for use as a baby wipe
- Do not use in genital area or on damaged skin

Inactive ingredients

Aloe Barbadensis Leaf Extract, Citrus Paradisi (Grapefruit) Peel Oil, Ethyl Butyrate, Ethyl Hydroxypyrone, Furaneol, Gamma-Undecalactone, Glycerin, Grapefruit Mercaptan, Limonene, Methylbenzyl Acetate, Neral, Triethyl Citrate, Water